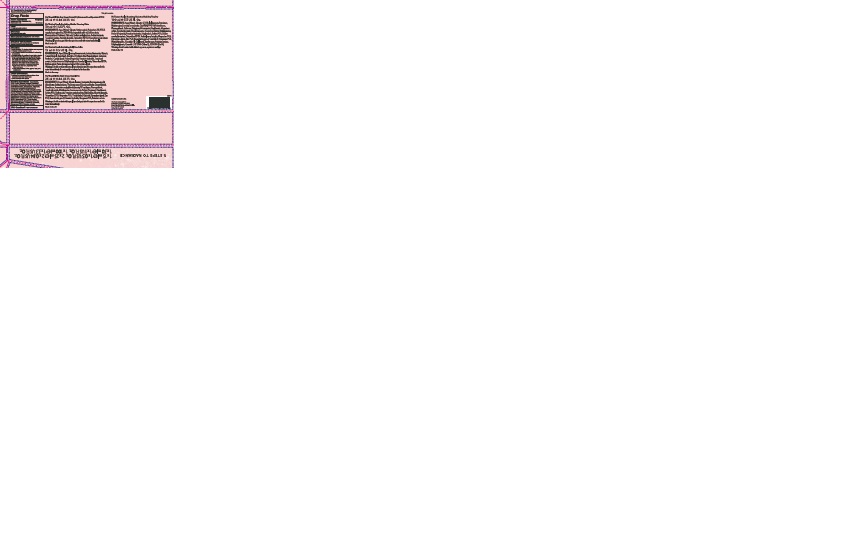 DRUG LABEL: No7 Beautiful Skin Day Cream  Normal Dry SPF 15
NDC: 11489-132 | Form: CREAM
Manufacturer: BCM Ltd
Category: otc | Type: HUMAN OTC DRUG LABEL
Date: 20180520

ACTIVE INGREDIENTS: AVOBENZONE 0.75 g/25 g; OCTOCRYLENE 1 g/25 g; OCTISALATE 0.5 g/25 g
INACTIVE INGREDIENTS: WATER; GLYCERIN; ALKYL (C12-15) BENZOATE; DIMETHICONE; ISOSTEARYL ISOSTEARATE; CETEARYL GLUCOSIDE; ALUMINUM STARCH OCTENYLSUCCINATE; TRIBEHENIN; POTASSIUM CETYL PHOSPHATE; AMMONIUM ACRYLOYLDIMETHYLTAURATE/VP COPOLYMER; PHENOXYETHANOL; CETOSTEARYL ALCOHOL; SHEA BUTTER; METHYLPARABEN; DIMETHICONOL (40 CST); ETHYLPARABEN; DIPROPYLENE GLYCOL; XANTHAN GUM; ASCORBYL GLUCOSIDE; EDETATE SODIUM; BIOSACCHARIDE GUM-1; TERT-BUTYL ALCOHOL; POTASSIUM HYDROXIDE; MANGANESE PCA; POTASSIUM SORBATE; ROSA CANINA FRUIT OIL

No7 Beautiful Skin Day Cream Normal Dry Sunscreen Broad Spectrum SPF 15

Carton Active Ingredients Section

Active ingredients

Avobenzone 3%

Octisalate 2%

Octocrylene 4%

Uses

Uses - helps prevent sunburn

Warnings

For external use only

Do not use on damaged or broken skin

When using this product keep out of eyes. Rinse with water to remove.

Ask a doctor

Stop use and ask a doctor if rash occurs

Keep out of reach of children

If swallowed, get medical help or contact a Poison Control Center right away

Directions

Apply liberally 15 minutes before sun exposure

reapply at least every 2 hours

use a water resistant sunscreen if swimming or sweating

children under 6 months of age: Ask a doctor

Sun Protection Measures. Spending time in the sun increases your risk of skin cancer and early skin aging.

To decrease this risk, regularly use a sunscreen with a Broad Spectrum SPF value of 15 or higher and other sun protection measures including:

Limit time in the sun, especially from 10 a.m - 2 p.m.

wear long-sleeved shirts,pants,hats and sunglasses.

Storage

Other information

Protect the product in this container from excessive heat and direct sun

Avoid contact with fabrics

Inactive ingredients

Aqua(Water), Glycerin, C12-15 alkyl bezoate, Isostearyl isostearate, Dimethicone, Cetearyl glucoside, Aluminum starch octenylsuccinate, Tribehenin, Ammonium acryloydimethyltaurate/VP copolymer, Phenoxyethanol, Butyrospermum parkii (Shea) butter, Potassium cetyl phosphate, Tocopheryl acetate, Rosa canina fruit oil, Cetearyl alcohol, Dimethiconol, Sodium PCA, Methyparaben, Parfum(Fragrance) Xanthan gum, Ethylparaben, Dipropylene glycol, Ascorbyl glucoside, Tetrasodium EDTA, Magnesium PCA, T-butyl alcohol, Zinc PCA, Biosaccharide gum-1, Potassium hydroxide, Manganese PCA, Silica, Potassium sorbate.

PATIENT COUNSELING INFORMATION

The Boots Company PLC Nottingham England NG2 3AA

Dist. in the USA by Boots Retail USA Inc.

New York NY 10005

www.boots.com/no7

Description

5 STEPS TO RADIANCE

1 x 15ml e 1 x 05 US Fl.Oz. 2 x 25ml e 2 x 0.84 Us Fl.Oz. 1 x 30ml e 1 x 1 US Fl.Ox 1 x 100ml e 1 x 3.3 Us Fl.Oz.